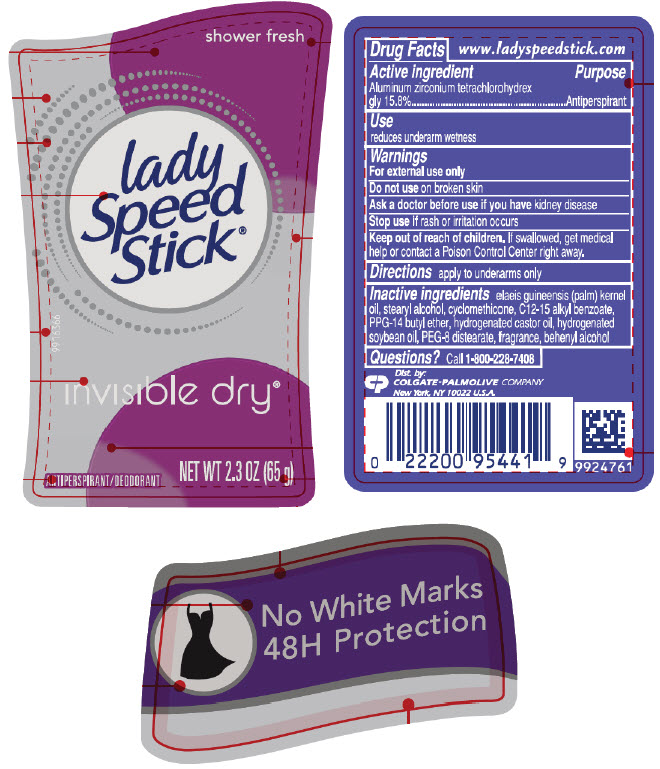 DRUG LABEL: Lady Speed Stick Invisible Dry Shower Fresh  Antiperspirant Deodorant
NDC: 35000-407 | Form: STICK
Manufacturer: COLGATE PALMOLIVE COMPANY
Category: otc | Type: HUMAN OTC DRUG LABEL
Date: 20210520

ACTIVE INGREDIENTS: ALUMINUM ZIRCONIUM TETRACHLOROHYDREX GLY 158 mg/1 g
INACTIVE INGREDIENTS: PALM KERNEL OIL; STEARYL ALCOHOL; CYCLOMETHICONE; ALKYL (C12-15) BENZOATE; PPG-14 BUTYL ETHER; HYDROGENATED CASTOR OIL; HYDROGENATED SOYBEAN OIL; PEG-8 DISTEARATE; DOCOSANOL

Lady Speed Stick® Invisible Dry Shower Fresh Antiperspirant Deodorant

Drug Facts

Active ingredient

Aluminum zirconium tetrachlorohydrex gly 15.8%

Purpose

Antiperspirant

Uses

- reduces underarm wetness
- 24H odor and wetness protection

Warnings

For external use only

Do not use on broken skin

Ask a doctor before use if you have kidney disease

Stop use if rash or irritation occurs

Keep out of reach of children. If swallowed, get medical help or contact a Poison Control Center right away.

Directions

apply to underarms only

Inactive ingredients

elaeis guineensis (palm) kernel oil, stearyl alcohol, cyclomethicone, C12-15 alkyl benzoate, PPG-14 butyl ether, hydrogenated castor oil, hydrogenated soybean oil, PEG-8 distearate, fragrance, behenyl alcohol

Questions?

Call 1-800-228-7408

Dist. by:
COLGATE-PALMOLIVE COMPANY
New York, NY 10022 U.S.A.

PRINCIPAL DISPLAY PANEL - 65 g Container Label

shower fresh

lady
Speed
Stick®

9916366

invisible dry®

ANTIPERSPIRANT/DEODORANT

NET WT 2.3 OZ (65 g)